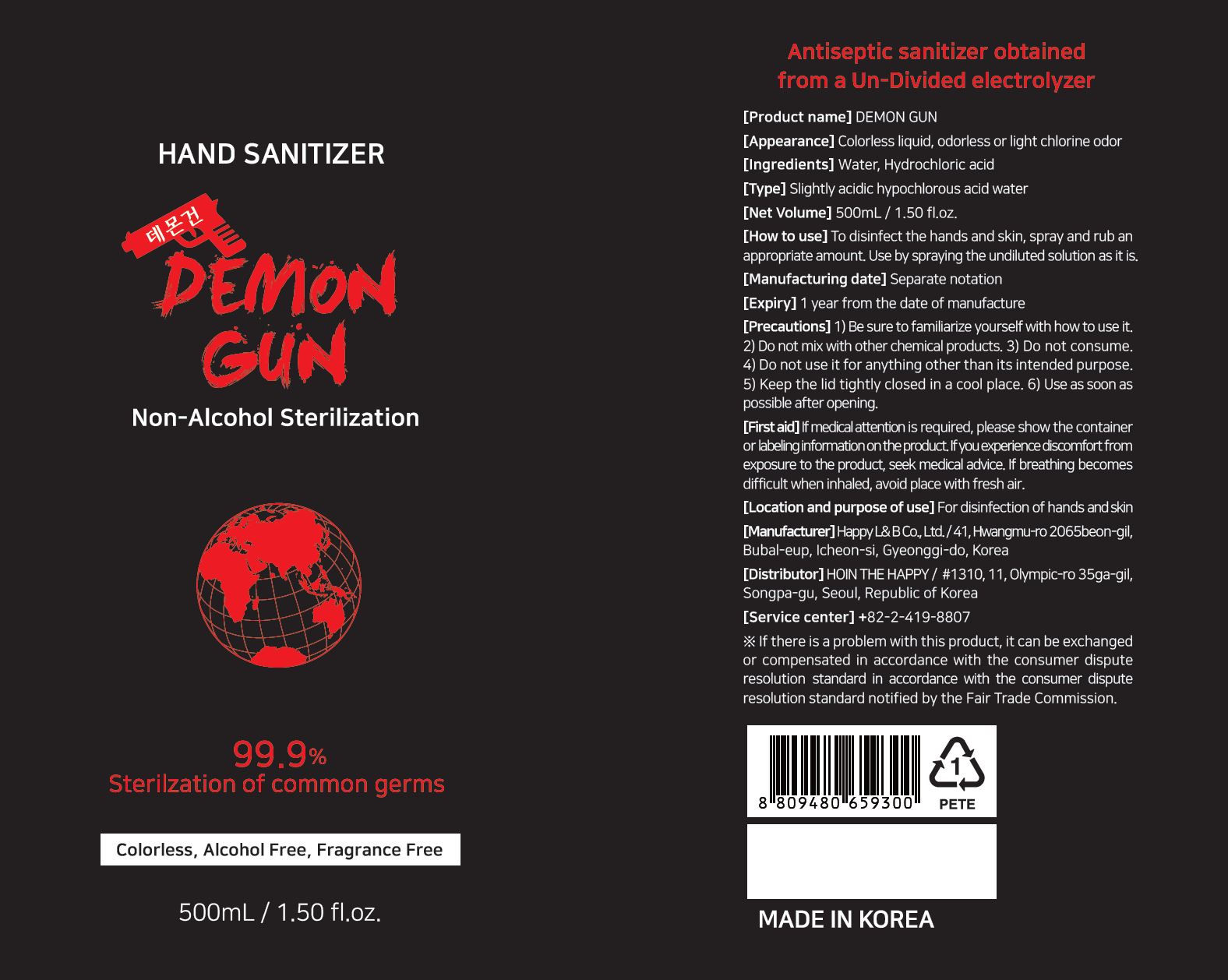 DRUG LABEL: DEMON GUN
NDC: 81939-0001 | Form: LIQUID
Manufacturer: HOIN THE HAPPY Co., Ltd.
Category: otc | Type: HUMAN OTC DRUG LABEL
Date: 20210522

ACTIVE INGREDIENTS: HYPOCHLOROUS ACID 0.0032 g/100 mL
INACTIVE INGREDIENTS: WATER

Drug Facts

ACTIVE INGREDIENT

Hydrochloric acid

INACTIVE INGREDIENT

water

PURPOSE

Antiseptic sanitizer

KEEP OUT OF REACH OF THE CHILDREN

INDICATIONS AND USAGE

To disinfect the hands and skin, spray and rub an appropriate amount. Use by spraying the undiluted solution as it is.

WARNINGS

1) Be sure to familiarize yourself with how to use it.
2) Do not mix with other chemical products. 3) Do not consume.
4) Do not use it for anything other than its intended purpose.
5) Keep the lid tightly closed in a cool place. 6) Use as soon as possible after opening.

DOSAGE AND ADMINISTRATION

external use only